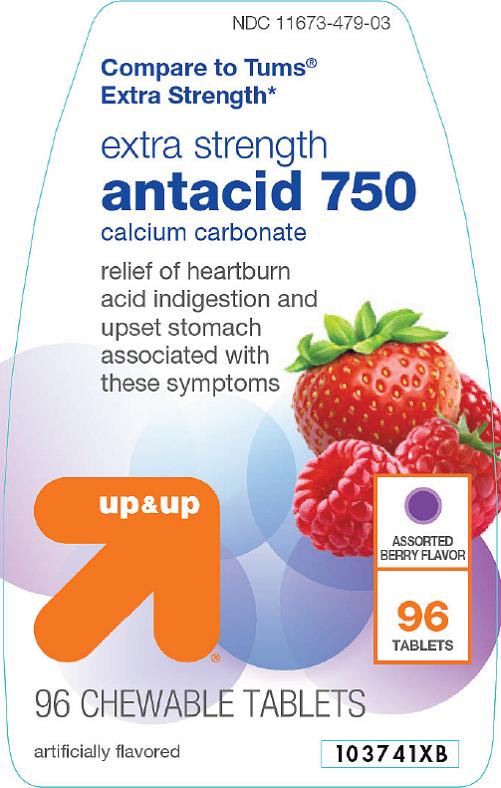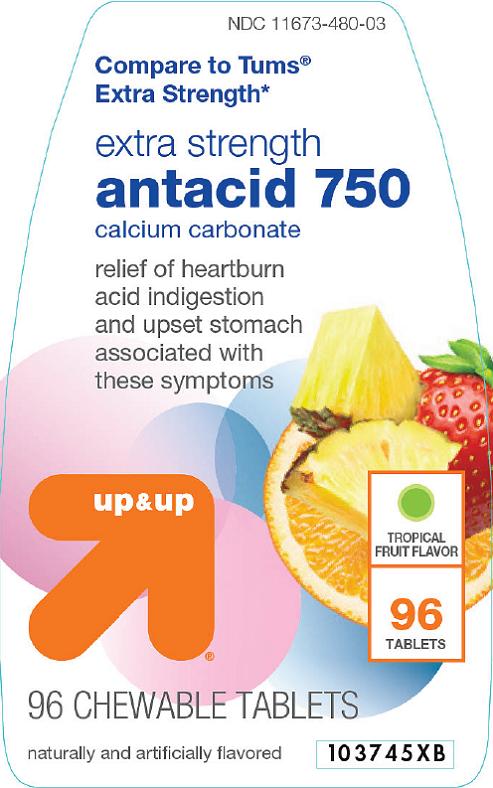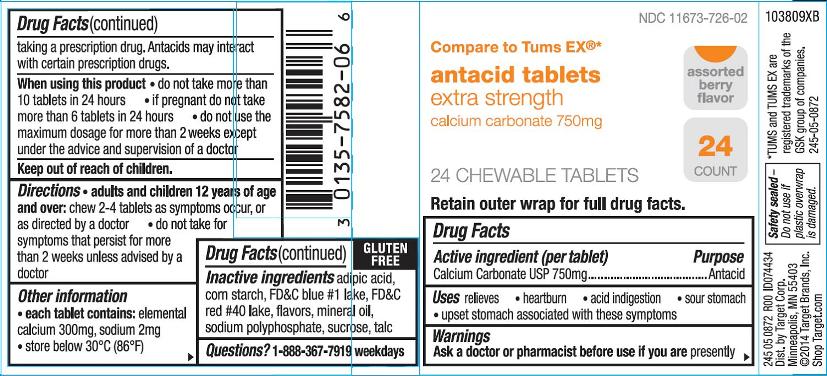 DRUG LABEL: ANTACID

NDC: 11673-479 | Form: TABLET, CHEWABLE
Manufacturer: Target Corporation
Category: otc | Type: HUMAN OTC DRUG LABEL
Date: 20240321

ACTIVE INGREDIENTS: CALCIUM CARBONATE 750 mg/1 1
INACTIVE INGREDIENTS: SUCROSE; STARCH, CORN; TALC; MINERAL OIL; ADIPIC ACID; SODIUM POLYMETAPHOSPHATE; FD&C RED NO. 40; FD&C BLUE NO. 1; ALUMINUM OXIDE

Drug Facts

Active ingredient (per tablet)

Calcium Carbonate USP 750 mg

Purpose

Antacid

Uses

relieves

- heartburn
- acid indigestion
- sour stomach
- upset stomach associated with these symptoms

Warnings

Ask a doctor or pharmacist before use if you are

presently taking a prescription drug. Antacids may interact with certain prescription drugs.

When using this product

- do not take more than 10 tablets in 24 hours
- if pregnant do not take more than 6 tablets in 24 hours
- do not use the maximum dosage for more than 2 weeks except under the advice and supervision of a doctor

Directions

- adults and children 12 years of age and over:chew 2 – 4 tablets as symptoms occur, or as directed by a doctor
- do not take for symptoms that persist for more than 2 weeks unless advised by a doctor

Other information

- each tablet contains:elemental calcium 300mg, sodium 2mg
- store below 30oC (86oF)

Inactive ingredients (Assorted Berry)

adipic acid, corn starch, FD&C blue #1 lake, FD&C red #40 lake, flavors, mineral oil, sodium polyphosphate, sucrose, talc

Inactive ingredients (Assorted Tropical Fruit)

corn startch, FD&C red #40 lake, FD&C yellow #5(tartrazine) lake, FD&C yellow #6 lake, flavors, mineral oil, sodium polyphosphate, sucrose, talc

Questions?

1-888-367-7919 weekdays

Principal Display Panel

NDC 11673-479-03

extra strength

antacid 750

calcium carbonate

Compare to Tums®Extra Strength*

relief of heartburn

acid indigestion and

upset stomach

associated with

these symptoms

up&up®

ASSORTED BERRY FLAVOR

96 CHEWABLE TABLETS

artificially flavored

Safety sealed – Do not use if printed inner seal beneath cap is missing or broken.

*TUMS®is a registered trademark of the GSK group of companies.

245 05 0459 R00 ID285492

Distributed by Target Corporation

Minneapolis, MN 55403

©2015 Target Brands, Inc.

Shop Target.com

GLUTEN FREE

103741XB (front label)

103740XB (back label)

Principal Display Panel

NDC 11673-480-03

extra strength

antacid 750

calcium carbonate

Compare to Tums®Extra Strength*

relief of heartburn

acid indigestion and

upset stomach

associated with

these symptoms

up&up®

TROPICAL FRUIT FLAVOR

96 CHEWABLE TABLETS

Naturally and artificially flavored

Safety sealed – Do not use if printed inner seal beneath cap is missing or broken.

*TUMS®is a registered trademark of the GSK group of companies.

245 05 0458 R00 ID285492

Distributed by Target Corporation

Minneapolis, MN 55403

©2015 Target Brands, Inc.

Shop Target.com

GLUTEN FREE

103745XB (front label)

103744XB (back label)

Principal Display Panel

NDC 11673-726-02

antacid tablets

extra strength

calcium carbonate 750mg

Compare to Tums EX®*

Assorted berry flavor

24 count

24 CHEWABLE TABLETS

Retain outer wrap for full drug facts.

GLUTEN FREE

245 05 0872 R00 ID074434

Dist. By Target Corp.

Minneapolis, MN 55403

©2014 Target Brands, Inc.

Shop Target.com

Safety sealed-Do not use if plastic overwrap is damaged.

*TUMS and TUMS EX are registered trademarks of the GSK group of companies.

245-05-0872

103809XB